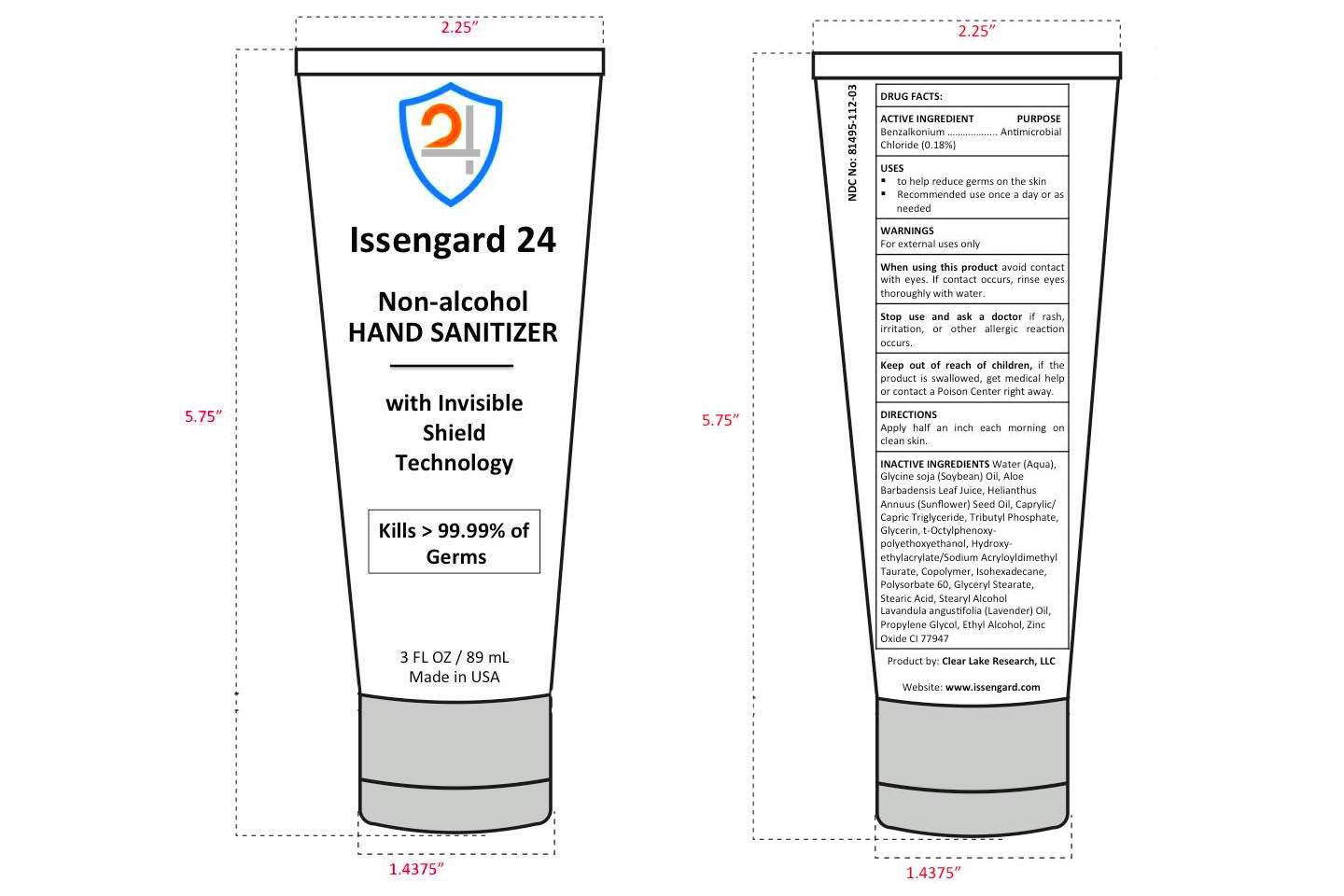 DRUG LABEL: ISSENGARD 24 HAND SANITIZER 3 oz
NDC: 81495-112 | Form: CREAM
Manufacturer: Clear Lake Research, LLC
Category: otc | Type: HUMAN OTC DRUG LABEL
Date: 20211230

ACTIVE INGREDIENTS: BENZALKONIUM CHLORIDE 0.18 mg/100 mL
INACTIVE INGREDIENTS: HYDROXYETHYL ACRYLATE/SODIUM ACRYLOYLDIMETHYL TAURATE COPOLYMER (45000 MPA.S AT 1%); MEDIUM-CHAIN TRIGLYCERIDES; STEARYL ALCOHOL; LAVENDER OIL; GLYCERIN; SUNFLOWER OIL; TRI-N-BUTYL PHOSPHATE; STEARIC ACID; ZINC OXIDE; ALCOHOL; WATER; POLYSORBATE 60; SOYBEAN OIL; OCTOXYNOL-1; ISOHEXADECANE; GLYCERYL MONOSTEARATE; ALOE VERA LEAF; PROPYLENE GLYCOL

DRUG FACTS

ACTIVE INGREDIENTS

Benzalkonium Chloride, 0.18%

PURPOSE SECTION

Antimicrobial

WARNINGS

For external uses only

USES

- to help reduce germs on the skin
- Recommended use once a day or as needed

WHEN USING SECTION

When using this product avoid contact with eyes. If contact occurs, rinse eyes thoroughly with water.

Stop use and ask a doctor if rash, irritation, or other allergic reaction occurs

KEEP OUT OF REACH OF CHILDREN SECTION

Keep out of reach of children, if the product is swallowed, get medical help or contact a Poison Center right away.

DIRECTIONS

Apply half an inch each morning on clean skin

INACTIVE INGREDIENTS

Water (Aqua), Glycine soja (Soybean) Oil, Aloe Barbadensis Leaf Juice, Helianthus Annuus (Sunflower) Seed Oil, Caprylic/Capric Triglyceride, Tributyl Phosphate, Glycerin, t-Octylphenoxy-polyethoxyethanol, Hydroxy- ethylacrylate/Sodium Acryloyldimethyl Taurate, Copolymer, Isohexadecane, Polysorbate 60, Glyceryl Stearate, Stearic Acid, Stearyl Alcohol, Lavandula angustifolia (Lavender) Oil, Propylene Glycol, Ethyl Alcohol, Zinc Oxide CI 77947

PRINCIPAL DISPLAY PANEL - 89 mL

Issengard 24

Non-alcohol HAND SANITIZER

with Invisible Shield Technology

Kills > 99.99% of Germs

3 FL OZ / 89 mL

Made in USA

Product by: Clear Lake Research, LLC

www.issengard.com